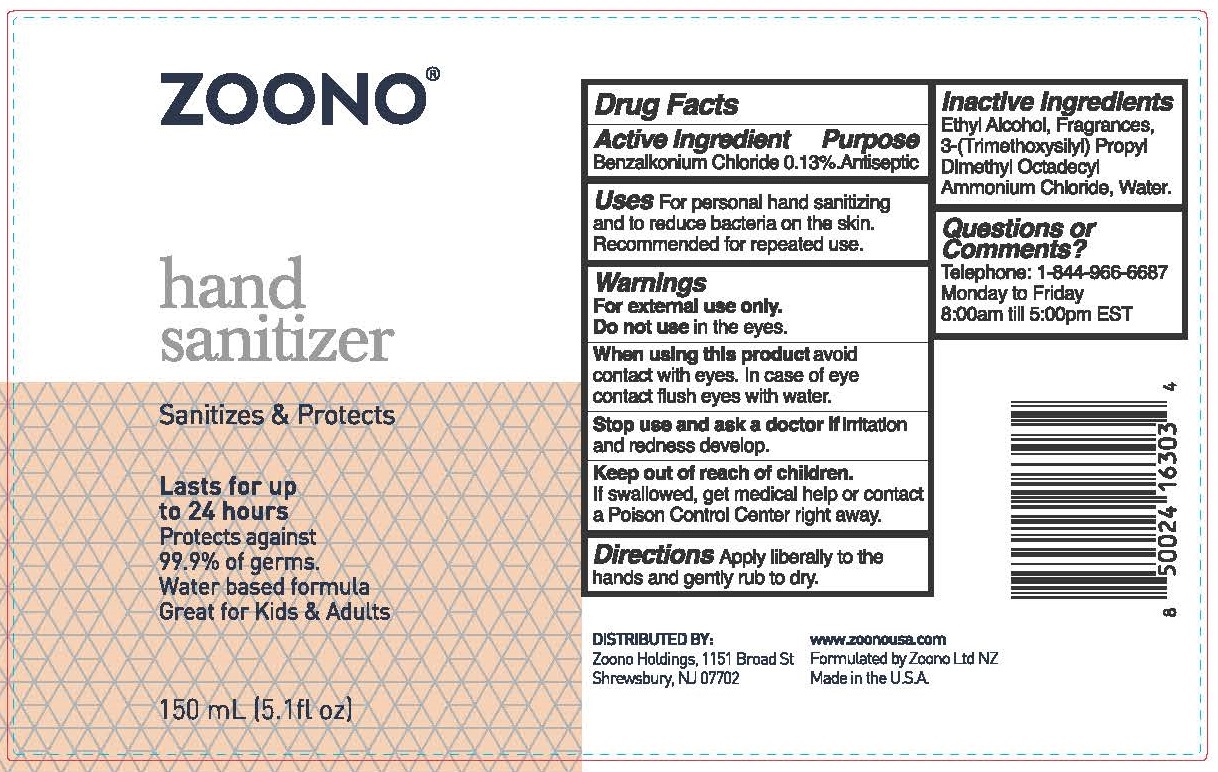 DRUG LABEL: Zoono Hand Sanitizer
NDC: 69221-203 | Form: SOLUTION
Manufacturer: Zoono Holdings USA
Category: otc | Type: HUMAN OTC DRUG LABEL
Date: 20250828

ACTIVE INGREDIENTS: BENZALKONIUM CHLORIDE 0.13 g/100 mL
INACTIVE INGREDIENTS: WATER

Zoono Hand Sanitizer

Active Ingredient

Benzalkonium Chloride 0.13%

Purpose:

Antiseptic

Uses:

For Personal hand sanitizing and to reduce bacteria on the skin. Recommended for repeated use.

Warnings:

For external use only.

Do not use in the eyes

When using this product avoid contact with eyes. In case of eye contact flush eyes with water.

Stop use and ask a doctor if irritation and redness develops.

Keep out of reach of children. If swallowed, get medical help or contact a Poison Control Center right away.

Inactive Ingredients:

Ethyl alcohol, Fragrances, Silica Complex (3-Trimethoxysilyl Propyl Dimethyl Octadecyl Ammonium Chloride), Water

Questions?

Telephone 1-844-966-6687 Monday through Friday 8:00am till 5:00pm EST

Directions:

Apply liberally to hands and gently rub until dry.